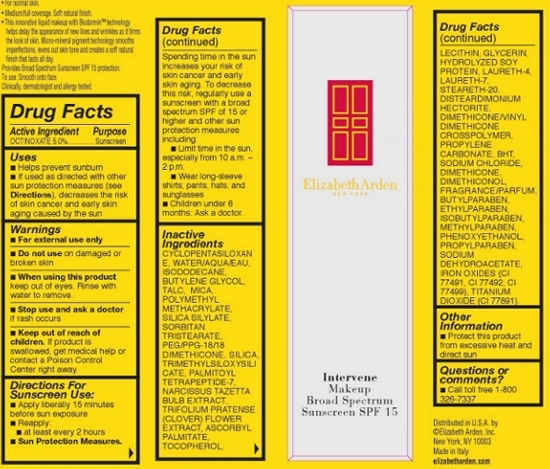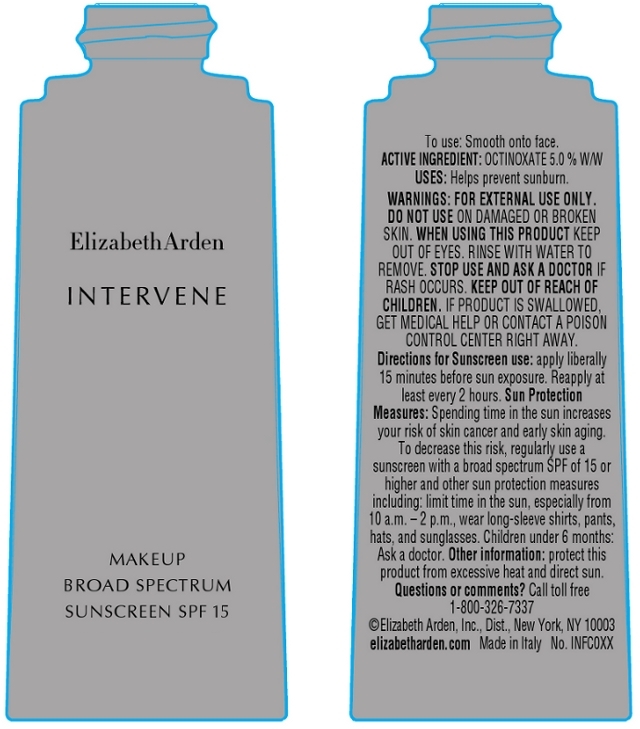 DRUG LABEL: Intervene Makeup Broad Spectrum Sunscreen SPF 15 Soft Cameo
NDC: 67938-1079 | Form: CREAM
Manufacturer: Elizabeth Arden, Inc
Category: otc | Type: HUMAN OTC DRUG LABEL
Date: 20130711

ACTIVE INGREDIENTS: OCTINOXATE 1.5 g/30 g
INACTIVE INGREDIENTS: WATER; ISODODECANE; BUTYLENE GLYCOL; TALC; SORBITAN TRISTEARATE; SILICON DIOXIDE; MICA; PHENOXYETHANOL; DIMETHICONE; SODIUM CHLORIDE; GLYCERIN; PROPYLENE CARBONATE; LAURETH-7; SODIUM DEHYDROACETATE; METHYLPARABEN; ETHYLPARABEN; BUTYLPARABEN; NARCISSUS TAZETTA BULB; PROPYLPARABEN; ISOBUTYLPARABEN; LAURETH-4; .ALPHA.-TOCOPHEROL; ASCORBYL PALMITATE; STEARETH-20; BUTYLATED HYDROXYTOLUENE; TRIFOLIUM PRATENSE FLOWER; PALMITOYL TETRAPEPTIDE-7

BC1079

DESCRIPTION

For normal skin. Medium/full coverage. Soft natural finish. This innovative liquid makeup with Biodormin technology helps delay the appearance of new lines and wrinkles as it firms the look of skin. Micro-mineral pigment technology smooths imperfections, evens out skin tone and creates a soft natural finish that lasts all day.

INDICATIONS AND USAGE

To Use: Smooth on to face.

Directions For Sunscreen Use: Apply liberally 15 minutes before sun exposure. Reapply: at least every 2 hours. Sun Protection Measures: Spending time in the sun increases your risk of skin cancer and early skin aging. To decrease this risk, regularly use a sunscreen with a broad spectrum SPF of 15 or higher and other sun protection measures including: Limit time in the sun, especially from 10 a.m. – 2 p.m. Wear long-sleeve shirts, pants, hats, and sunglasses. Children under 6 months: Ask a doctor.

WARNINGS

For external use only

Do not use on damaged or broken skin

When using this product keep out of eyes. Rinse with water to remove.

Stop use and ask a doctor if rash occurs.

OTC - ACTIVE INGREDIENT

Active Ingredient: Octinoxate 5.0%.

INACTIVE INGREDIENT

Other Ingredients: Cyclopentasiloxane, Water/Aqua/Eau, Isododecane, Butylene Glycol, Talc, Mica, Polymethyl Methacrylate, Silica Silylate, Sorbitan Tristearate, PEG/PPG-18/18 Dimethicone, Silica, Trimethylsiloxysilicate, Palmitoyl Tetrapeptide-7, Narcissus Tazetta Bulb Extract, Trifolium Pratense (Clover) Flower Extract, Ascorbyl Plamitate, Tocopherol, Lecithin, Clycerin, Hydolyzed Soy Protein, Laureth-4, Laureth-7, Steareth-20, Disteardimonium Hectorite, Deimethicone/Vinyl Dimethicone Crosspolymer, Propylene Carbonate, BHT, Sodium Chloride, Dimethicone, Dimethiconol, Fragrance/Parfum, Butylparaben, Ethylparaben, Isobutylparaben, Methylparaben, Phenoxyethanol, Propylparaben, Sodium Dehydroacetate, Iron Oxides (CI 77491, CI 77492, CI 77499), Titanium Dioxide (CI77891).

DOSAGE & ADMINISTRATION

Smooth on to face.

Keep out of reach of children. If product is swallowed, get medical help or contact a Poison Control Center right away.

OTC - PURPOSE

Provides SPF 15 Sun Protection.

OTC - WHEN USING

Keep out of eyes.